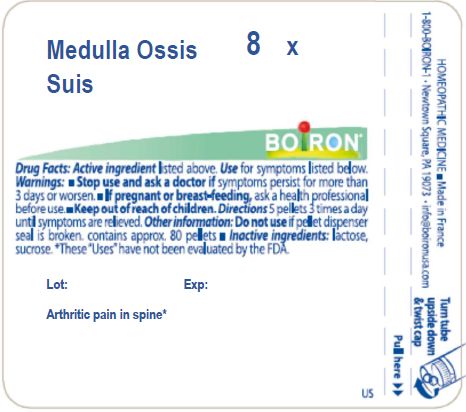 DRUG LABEL: MEDULLA OSSIS SUIS
NDC: 0220-3329 | Form: PELLET
Manufacturer: BOIRON
Category: homeopathic | Type: HUMAN OTC DRUG LABEL
Date: 20231114

ACTIVE INGREDIENTS: SUS SCROFA BONE MARROW 8 [hp_X]/8 [hp_X]
INACTIVE INGREDIENTS: SUCROSE; LACTOSE, UNSPECIFIED FORM

MEDULLA OSSIS SUIS

ACTIVE INGREDIENT

MEDULLA OSSIS SUIS HPUS

8X

PURPOSE

Arthritic pain in spine

INDICATIONS AND USAGE

Arthritic pain in spine

STOP USE IF SYMPTOMS PERSIST FOR MORE THAN 3 DAYS OR WORSEN

PREGNANCY OR BREAST FEEDING

ASK A HEALTH PROFESSIONAL BEFORE USE

KEEP OUT OF REACH OF CHILDREN

DOSAGE AND ADMINISTRATION

5 PELLETS 3 TIMES A DAY UNTIL SYMPTOMS ARE RELIEVED

DO NOT USE IF PELLET DISPENSER IS BROKEN.

CONTAINS APPROX. 80 PELLETS

INACTIVE INGREDIENT

LACTOSE, SUCROSE

QUESTIONS

1-800-BOIRON-1

Newtown Square, PA 19073-3267

info@boironusa.com

These "Uses" have not been evaluated by the FDA.